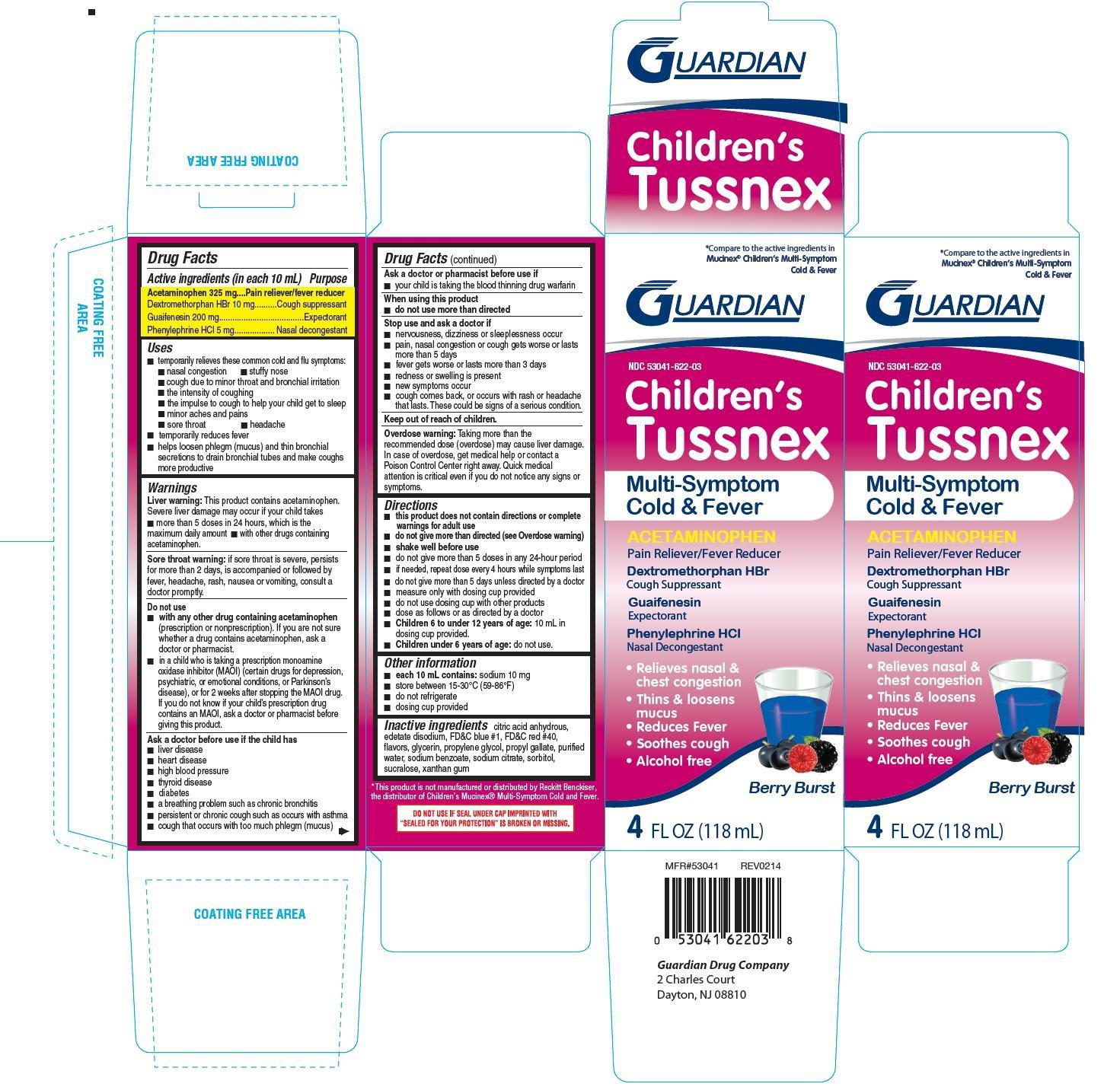 DRUG LABEL: Childrens Tussnex
NDC: 53041-622 | Form: LIQUID
Manufacturer: Guardian Drug Company
Category: otc | Type: HUMAN OTC DRUG LABEL
Date: 20241219

ACTIVE INGREDIENTS: ACETAMINOPHEN 325 mg/10 mL; DEXTROMETHORPHAN HYDROBROMIDE 10 mg/10 mL; PHENYLEPHRINE HYDROCHLORIDE 5 mg/10 mL; GUAIFENESIN 200 mg/10 mL
INACTIVE INGREDIENTS: ANHYDROUS CITRIC ACID; EDETATE DISODIUM; FD&C BLUE NO. 1; FD&C RED NO. 40; GLYCERIN; PROPYLENE GLYCOL; PROPYL GALLATE; WATER; SODIUM BENZOATE; SODIUM CITRATE; SORBITOL; SUCRALOSE; XANTHAN GUM

Childrens Tussnex Multi-Symptom Cold and Fever

Active ingredients (in each 10 mL)

Acetaminophen 325 mg

Dextromethorphan HBr 10 mg

Guaifenesin 200 mg

Phenylephrine HCl 5 mg

Purpose

Pain reliever/fever reducer

Cough suppressant

Expectorant

Nasal decongestant

Uses

- temporarily relieves these common cold and flu symptoms:
- nasal congestion
- stuffy nose
- cough due to minor throat and minor bronchial irritation
- the intensity of coughing
- the impulse to cough to help your child get to sleep
- minor aches and pains
- sore throat
- headache
- temporarily reduces fever
- helps loosen phlegm (mucus) and thin bronchial secretions to drain bronchial tubes and make coughs more productive

Warnings

- Liver warning: This product contains acetaminophen. severe liver damage may occur if your child takes
- more than 5 doses in 24 hours, which is maximum daily amount
- with other drugs containing acetaminophen
- Sore throat warning: if sore throat is severe, persists for more than 2 days, is accompanied or followed by fever, headache, rash, nausea, vomiting, consult a doctor promptly.

Do not use

- with any other drug containing acetaminophen (prescription or non prescription). If you are not sure whether a drug contains acetaminophen, ask a doctor or pharmacist.
- in a child who is taking a prescription monoamine oxidase inhibitor (MAOI) (certain drugs for depression, psychiatric, or emotional conditions or parkinson's disease), or for 2 weeks after stopping the MAOI drug. If you do not know if your prescription drug contains an MAOI, ask a doctor or pharmacist before giving this product.

Ask a doctor before use if the child has

- liver disease
- heart disease
- high blood pressure
- thyroid disease
- diabetes
- a breathing problem such as chronic bronchitis
- persistent or chronic cough such as occurs with smoking, asthma, chronic bronchitis or emphysema
- cough that occurs with too much phlegm (mucus)

Ask a doctor or pharmacist before use if

you are taking the blood thinning drug warfarin

When using this product

- do not use more than directed

Stop use and ask a doctor if

- nervousness, dizziness or sleeplessness occur
- pain, nasal congestion or cough gets worse or lasts more than 5 days
- fever gets worse or lasts more than 3 days
- redness or swelling is present
- new symptoms occur
- cough comes back, or occurs with rash or persistent headache. These could be signs of a serious condition.

Keep out of reach of children.

Overdose warning: Taking more than the recommended dose (overdose) may cause liver damage. In case of overdose, get medical help or contact a poison control center right away. Quick medical attention is critical for adults as well as for children even if you do not notice any signs or symptoms.

Directions

- this product does not contain directions or complete warnings for adult dose
- do not take more than directed (see overdose warning)
- shake well before use
- do not take more than 5 doses in any 24 hour period
- if needed, repeat dose every 4 hours while symptoms last
- do not give more than 5 days unless directed by a doctor
- measure only with dosing cup provided
- do not use dosing cup with other products
- dose as follows or as directed by a doctor
- Children 6 to under 12 years of age: 10 mL in dosing cup provided
- Children under 6 years of age: Do not use

Other information

- each 10 mL contains: sodium 10 mg
- store between 15-30oC(59-86oF)
- do not refrigerate
- dosing cup provided

Inactive ingredients

citric acid anhydrous, edetate disodium, FD and C blue 1, FD and C red 40, flavors, glycerin, propylene glycol, propyl gallate, purified water, sodium benzoate, sodium citrate, sorbitol, sucralose, xanthan gum

PDP

Compare to the active ingredients in Mucinex Childrens Multi-symptom Cold and Fever

Childrens Tussnex Multi symptom Cold and Fever

Acetaminophen

Pain reliever / Fever Reducer

Dextromethorphan HBr

Cough Suppressant

Guaifenesin

Expectorant

Phenylephrine HCl

Nasal Decongestant

Relieves Nasal and chest congestion

Thins and loosens mucus

Reduces fever

Soothes cough

Alcohol Free